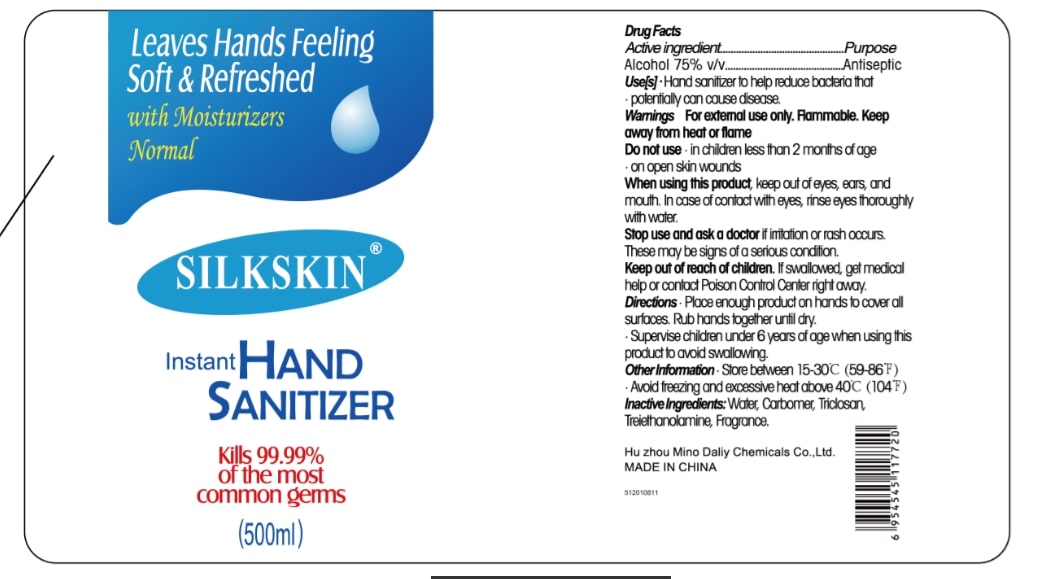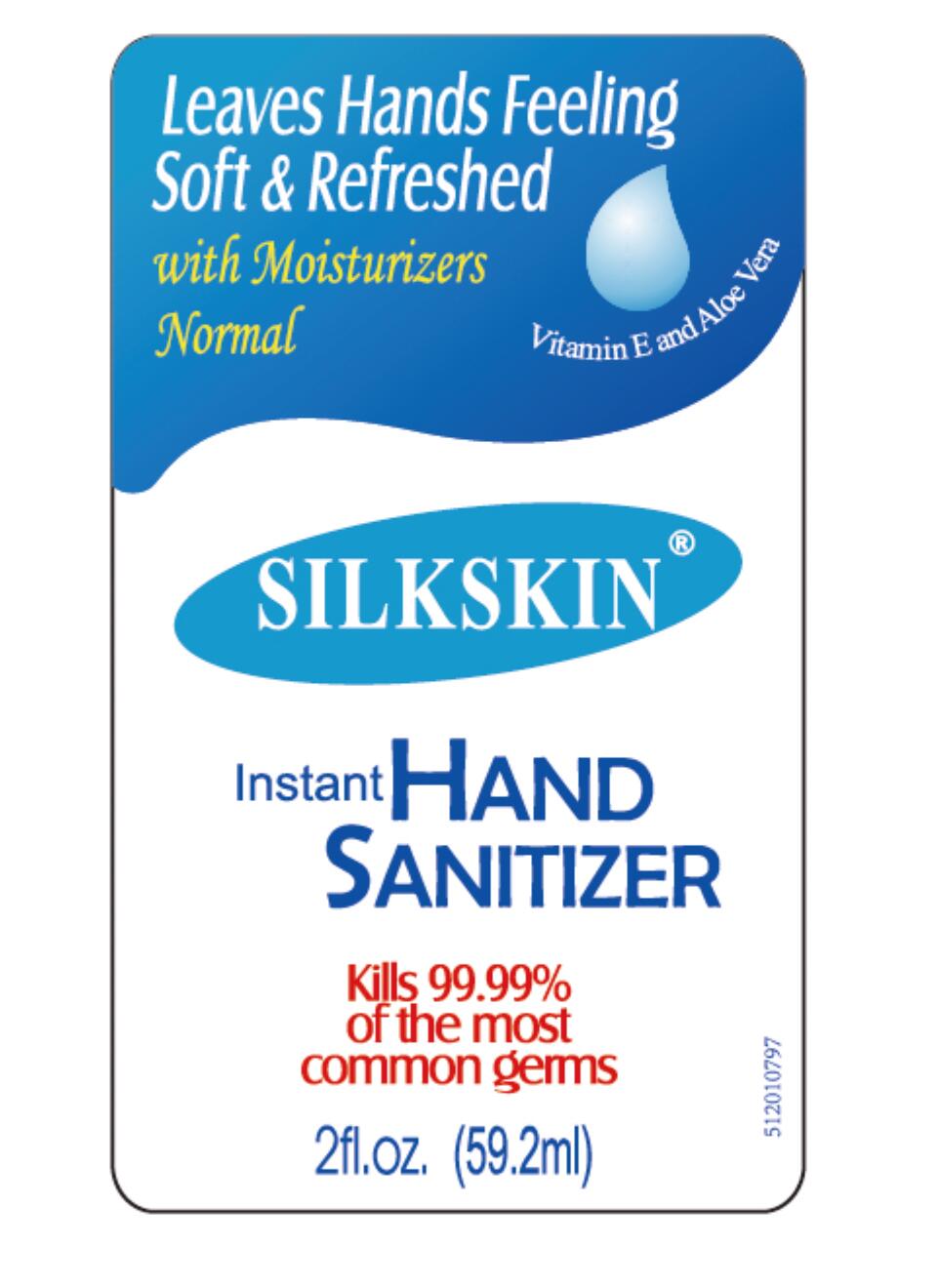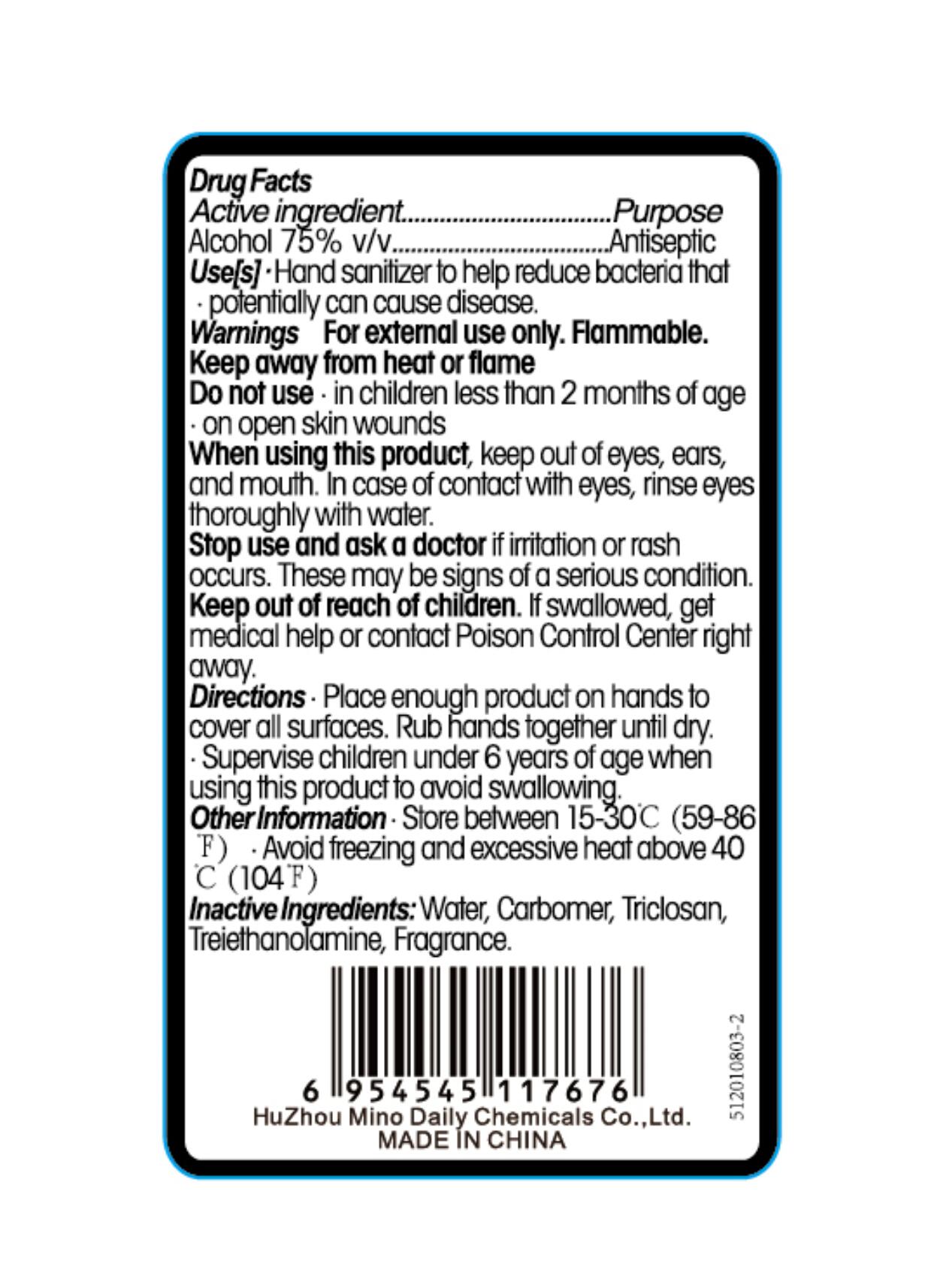 DRUG LABEL: SILKSKIN Instant Hand Sanitizer
NDC: 61696-001 | Form: GEL
Manufacturer: Huzhou Mino Daily Chemicals Co., Ltd.
Category: otc | Type: HUMAN OTC DRUG LABEL
Date: 20200922

ACTIVE INGREDIENTS: ALCOHOL 75 mL/100 mL
INACTIVE INGREDIENTS: WATER; CARBOMER HOMOPOLYMER, UNSPECIFIED TYPE; TRICLOSAN; TROLAMINE

Active ingredient

Alcohol 75% v/v

Purpose

Antiseptic

Use[s]

Hand sanitizer to help reduce bacteria that potentially can cause disease.

Warnings

For external use only. Flammable. Keep away from heat or flame

Do not use

- in children less than 2 months of age
- on open skin wounds

When using this product, keep out of eyes, ears, and mouth. In case of contact with eyes, rinse eyes thoroughly with water.

Stop use and ask a doctor if irritation or rash occurs. These may be signs of a serious condition.

Keep out of reach of children. If swallowed, get medical help or contact Poison Control Center right away.

Directions

- Place enough product on hands to cover all surfaces. Rub hands together until dry.
- Supervise children under 6 years of age when using this product to avoid swallowing.

Other Information

- Store between 15-30°C (59-86°F)
- Avoid freezing and excessive heat above 40°C (104°F)

Inactive Ingredients:

Water, Carbomer, Triclosan, Triethanolamine, Fragrance.

PACKAGE LABEL

NDC 61696-001-01 (59.2 mL)

NDC 61696-001-02 (500 mL)